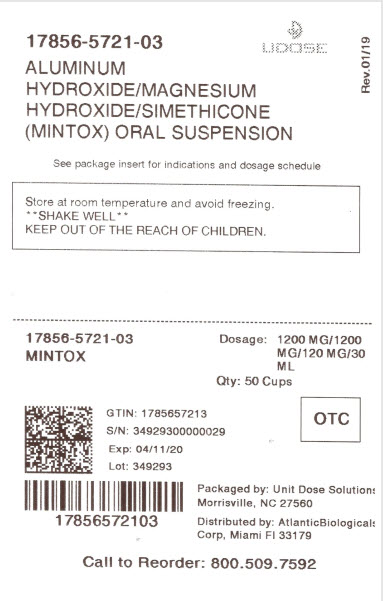 DRUG LABEL: MINTOX
                                    
NDC: 17856-5721 | Form: SUSPENSION
Manufacturer: ATLANTIC BIOLOGICALS CORP.
Category: otc | Type: HUMAN OTC DRUG LABEL
Date: 20210126

ACTIVE INGREDIENTS: ALUMINUM HYDROXIDE 200 mg/5 mL; MAGNESIUM HYDROXIDE 200 mg/5 mL; DIMETHICONE 20 mg/5 mL
INACTIVE INGREDIENTS: BENZYL ALCOHOL; BUTYLPARABEN; CARBOXYMETHYLCELLULOSE SODIUM; HYPROMELLOSES; CELLULOSE, MICROCRYSTALLINE; PROPYLPARABEN; WATER; SACCHARIN SODIUM; SORBITOL

Active ingredients (in each 5 mL teaspoonful)

Aluminum hydroxide 200 mg (equivalent to dried gel, USP)

Magnesium hydroxide 200 mg

Simethicone 20mg

Purposes

Antacid

Antigas

Uses

relieves

- heartburn
- sour stomach
- acid indigestion
- the symptoms referred to as gas

Warnings

Ask a doctor before use if you have

• kidney disease

• a magnesium-restricted diet

taking a prescription drug. Ask a doctor or pharmacist before use if you are

Antacids may interact with certain prescription drugs.

symptoms last more than 2 weeks Stop use and ask a doctor if

ask a health professional before use. If pregnant or breast-feeding,

Keep out of reach of children.

Directions

• shake well before use

• adults and children 12 years and older: take 2 to 4 teaspoonfuls four times a day, or as directed by a doctor

• do not take more than 16 teaspoonfuls in 24 hours or use the maximum dosage for more than 2 weeks

• children under 12 years: ask a doctor

Other information

• magnesium 85 mg, sodium 1 mg each 5 mL teaspoonful contains:

• store at room temperature

• protect from freezing

• keep tightly closed

• TAMPER-EVIDENT: Do not use if breakaway band on bottle is missing or broken.

Inactive ingredients

benzyl alcohol, butylparaben, carboxymethylcellulose sodium, flavor, hypromellose, microcrystalline cellulose, propylparaben, purified water, saccharin sodium, sorbitol solution